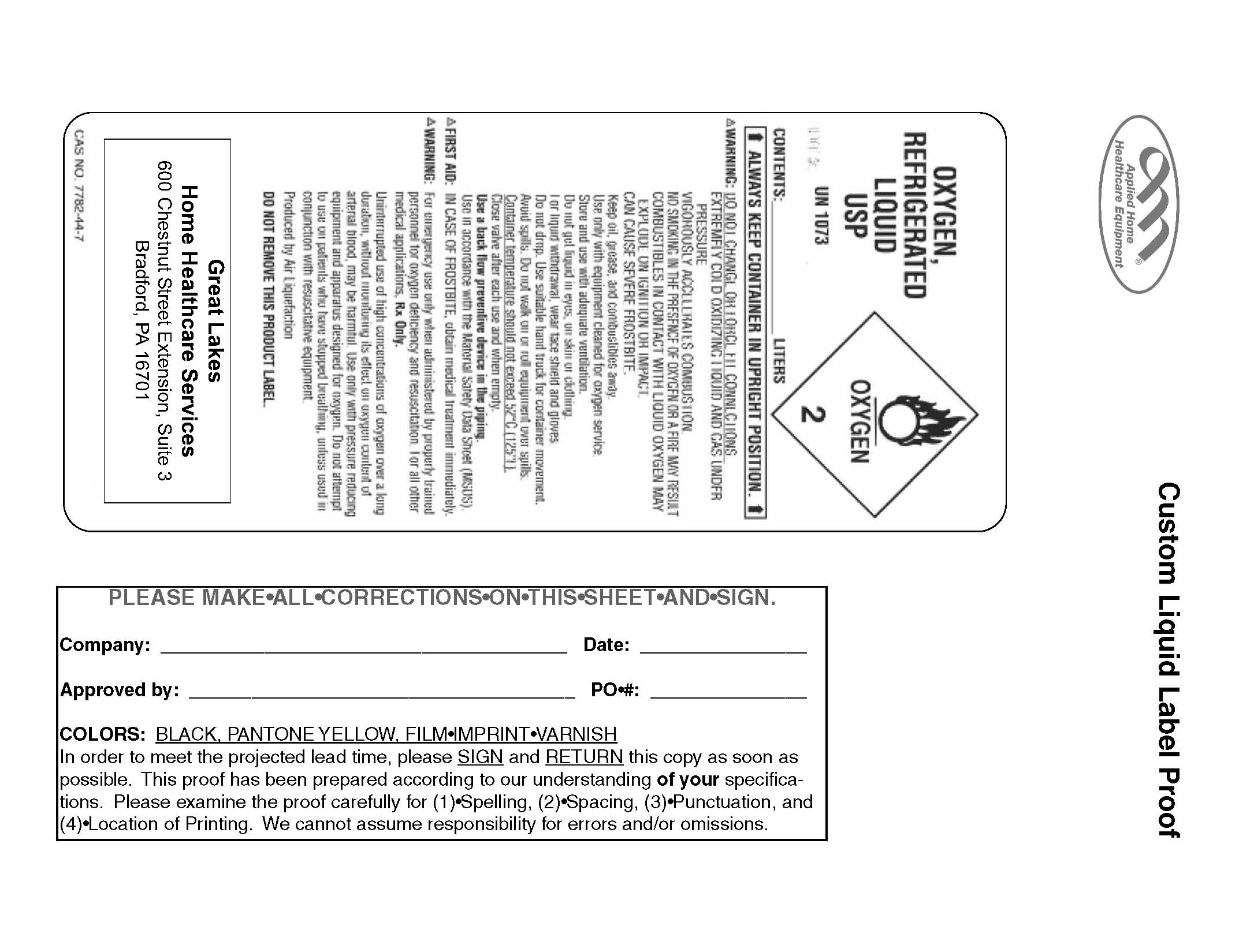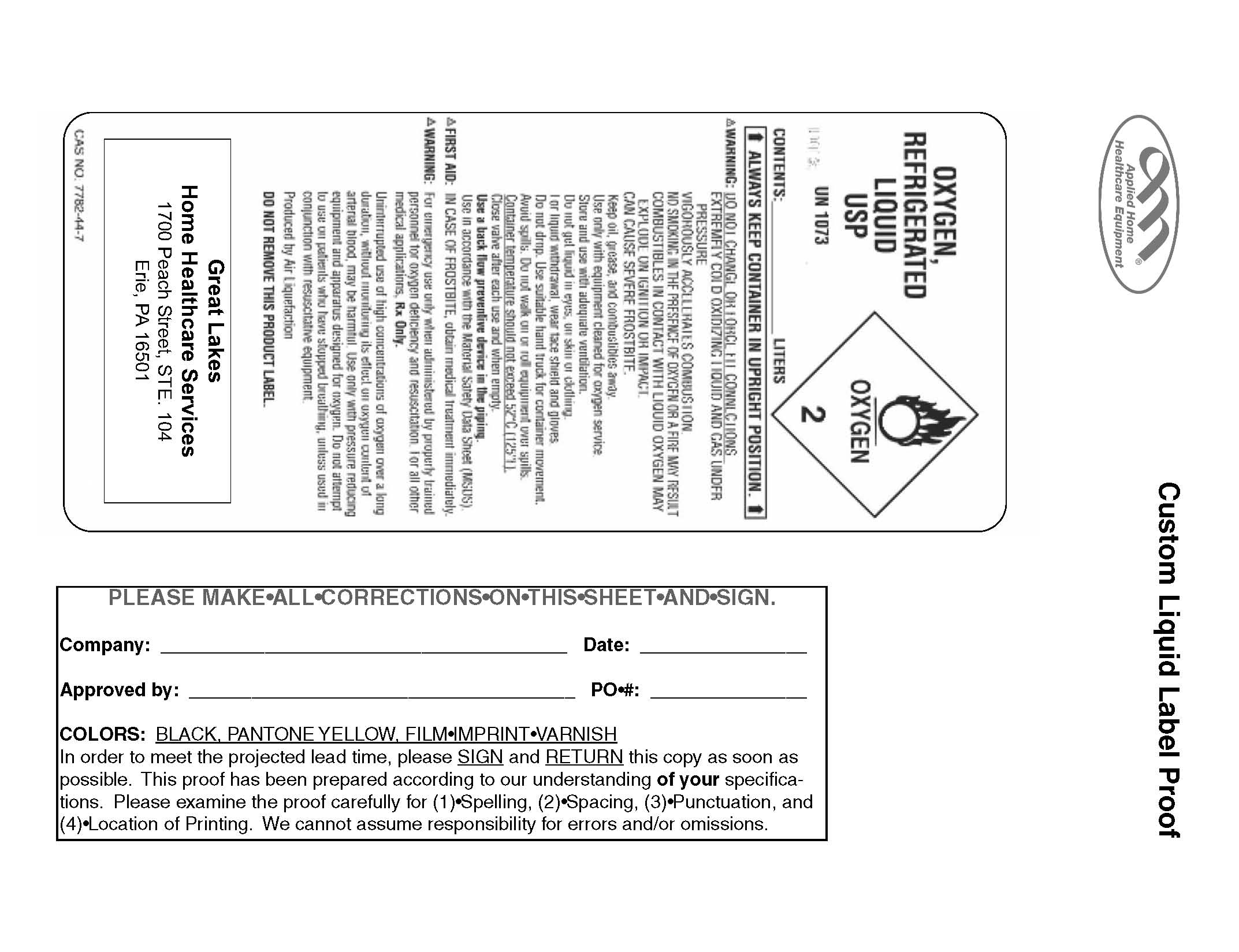 DRUG LABEL: Oxygen
NDC: 64454-0001 | Form: GAS
Manufacturer: Great Lakes Home Healthcare Services
Category: prescription | Type: HUMAN PRESCRIPTION DRUG LABEL
Date: 20091215

ACTIVE INGREDIENTS: Oxygen 99 L/100 L

Oxygen